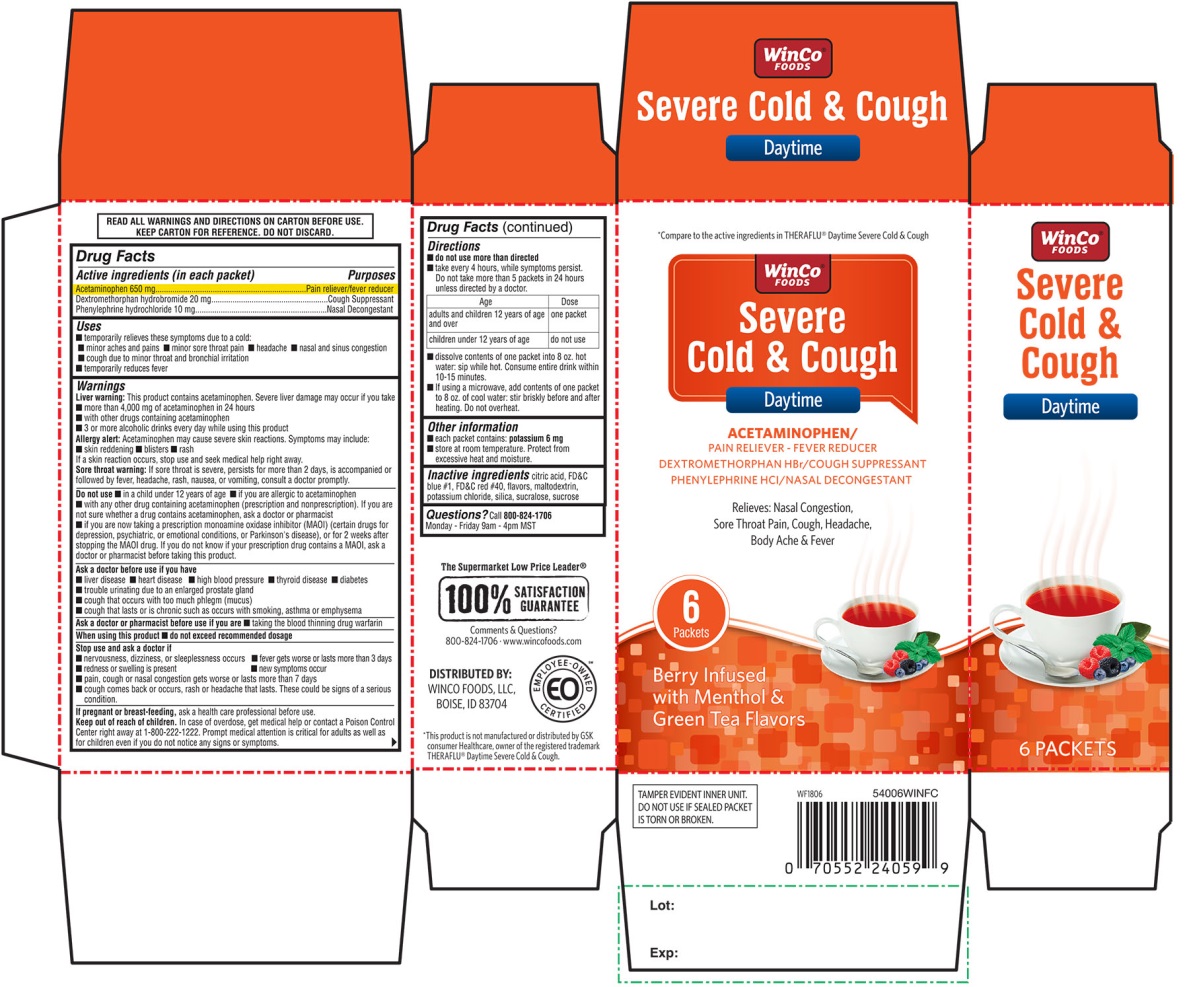 DRUG LABEL: Severe Cold and Cough Daytime
NDC: 67091-322 | Form: POWDER, FOR SOLUTION
Manufacturer: WinCo Foods, LLC
Category: otc | Type: HUMAN OTC DRUG LABEL
Date: 20251202

ACTIVE INGREDIENTS: ACETAMINOPHEN 650 mg/1 1; DEXTROMETHORPHAN HYDROBROMIDE 20 mg/1 1; PHENYLEPHRINE HYDROCHLORIDE 10 mg/1 1
INACTIVE INGREDIENTS: ANHYDROUS CITRIC ACID; FD&C BLUE NO. 1; FD&C RED NO. 40; MALTODEXTRIN; POTASSIUM CHLORIDE; SILICON DIOXIDE; SUCRALOSE; SUCROSE

WinCo Foods Severe Cold & Cough Daytime Berry Infused with Menthol & Green Tea Flavors 6 Packets

Active ingredient (in each packet)

Acetaminophen 650 mg

Dextromethorphan HBr 20 mg

Phenylephrine HCl 10 mg

Purposes

Pain reliever/fever reducer

Cough suppressant

Nasal decongestant

Uses

- temporarily relieves these symptoms due to a cold:
  - minor aches and pains
  - minor sore throat pain
  - headache
  - nasal and sinus congestion
  - cough due to minor throat and bronchial irritation
- temporarily reduces fever

Warnings

Liver warning:This product contains acetaminophen. Severe liver damage may occur if you take

- more than 4,000 mg of acetaminophen in 24 hours
- with other drugs containing acetaminophen
- 3 or more alcoholic drinks every day while using this product

Allergy alert:Acetaminophen may cause severe skin reactions. Symptoms may include:

- skin reddening
- blisters
- rash

If a skin reaction occurs, stop use and seek medical help right away

Sore throat warning:If sore throat is severe, persists for more than 2 days, is accompanied or followed by fever, headache, rash, nausea, or vomiting consult a doctor promptly.

Do not use

- in a child under 12 years of age
- if you are allergic to acetaminophen
- with any other drug containing acetaminophen (prescription or nonprescription). If you are not sure whether a drug contains acetaminophen, ask a doctor or a pharmacist.
- if you are now taking a prescription monoamine oxidase inhibitor (MAOI) (certain drugs for depression, psychiatric, or emotional conditions, or Parkinson's disease), or for 2 weeks after stopping the MAOI drug. If you do not know if your prescription drug contains an MAOI, ask a doctor or pharmacist before taking this product.

Ask doctor before use if you have

- liver disease
- heart disease
- high blood pressure
- thyroid disease
- diabetes
- trouble urinating due to an enlarged prostate gland
- cough that occurs with too much phlegm (mucus)
- cough that lasts or is chronic such as occurs with smoking, asthma or emphysema

Ask a doctor or pharmacist before use if you are

- taking the blood thinning drug warfarin

When using this product

- do not exceed recommended dosage

Stop use and ask a doctor if

- nervousness, dizziness, or sleeplessness occurs
- fever gets worse or lasts more than 3 days
- redness or swelling is present
- new symptoms occur
- pain, cough or nasal congestion gets worse or lasts more than 7 days
- cough comes back or occurs with rash or headache that lasts. These could be signs of a serious condition.

If pregnant or breast-feeding,

ask a health professional before use.

Keep out of reach of children.

In case of overdose, get medical help or contact a Poison Control Center right away at 1-800-222-1222. Prompt medical attention is critical for adults as well as for children even if you do not notice any signs or symptoms.

Directions

- do not use more than directed
- take every 4 hours, while symptoms persist. Do not take more than 5 packets in 24 hours unless directed by a doctor.

Age | Dose
adults and children 12 years of age and over | one packet
children under 12 years of age | do not use

- dissolve contents of one packet into 8 oz. hot water; sip while hot. Consume entire drink within 10-15 minutes.
- if using a microwave, add contents of one packet to 8 oz. of cool water; stir briskly before and after heating. Do not overheat.

Other information

- each packet contains : potassium 6 mg
- store at room temperature .Protect from excessive heat and moisture.

Inactive ingredients

citric acid, aspartame, FD&C blue # 1, FD&C red # 40, flavors, maltodextrin, potassium chloride, silica, sucralose, sucrose,

Questions or comments?

Call 800-824-1706

Monday-Friday 9am-4pm MST

Principal Display

*Compare to the active ingredients in THERAFLU®Daytime Severe Cold &Cold

WinCo FOODS

Severe Cold & Cough

Daytime

ACETAMINOPHEN – PAIN RELIEVER/FEVER REDUER

DEXTROMETHORPHAN HBr – COUGH SUPPRESSANT

PHENYLEPHRINE HCl – NASAL DECONGESTANT

- Relieves: Nasal Congestion, Sore Throat Pain, Cough, Headache, Body Ache & Fever

6 PACKETS

Berry Infused with Menthol & Green Tea Flavors

READ ALL WARNINGS AND DIRECTIONS ON CARTON BEFORE USE.

KEEP CARTON FOR REFERENCE. DO NOT DISCARD.

TAMPER EVIDENT INNER UNIT

DO NOT USE IF SEALED PACKET IS TORN OR BROKEN

The Supermarket Low price Leader®

100% SATISFACTION GUARANTEE

Comments & Questions?

800-824-1706 www.wincofoods.com

DISTRIBUTED BY:

WINCO FOODS, LLC,

BOISE, ID 83704

*This product is not manufactured or distributed by GSK consumer Healthcare, owner of the registered trademark THERAFLU®Daytime Severe Cold & Cough.